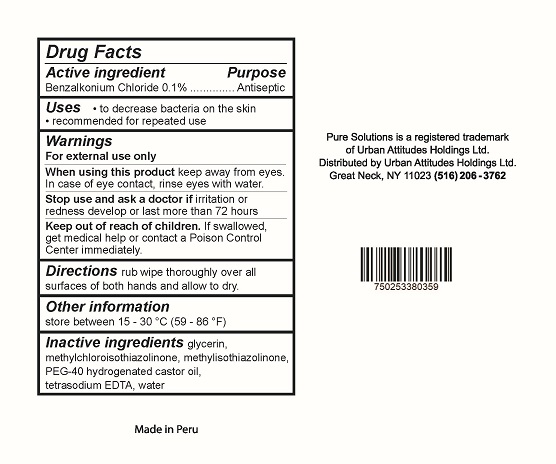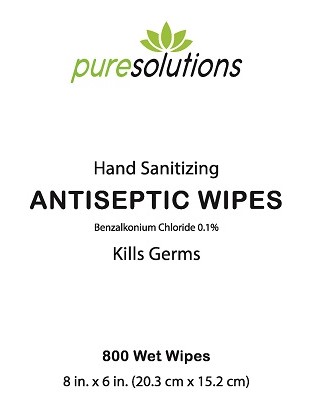 DRUG LABEL: Pure Solutions Antiseptic Wipes
NDC: 77185-004 | Form: CLOTH
Manufacturer: Urban Attitudes Holdings Ltd
Category: otc | Type: HUMAN OTC DRUG LABEL
Date: 20200828

ACTIVE INGREDIENTS: BENZALKONIUM CHLORIDE 0.1 g/100 mL
INACTIVE INGREDIENTS: EDETATE SODIUM; METHYLISOTHIAZOLINONE; METHYLCHLOROISOTHIAZOLINONE; POLYOXYL 40 HYDROGENATED CASTOR OIL; WATER; GLYCERIN

Pure Solutions Hand Sanitizing Wipes

Drug Facts

Active ingredient

Benzalkonium Chloride 0.1%

Purpose
Antiseptic

Uses

- to decrease bacteria on the skin
- recommended for repeated use

Warnings

For external use only

When using this product keep away from eyes. In case of eye contact, rinse eyes with water.

Stop use and ask a doctor if irritation or redness develop or last more than 72 hours.

Keep out of reach of children. If swallowed, get medical help or contact a Poison Control Center immediately.

Directions

rub wipe thoroughly over all sufaces of both hands and allow to dry

Other information

store between 15-30°C (59-86°F)

Inactive ingredients

glycerin, methylchloroisothiazolinone, methylisothiazonlinone, PEG-40 hydrogenated castor oil, tetrasodium EDTA, water

Pure Solutions is a registered trademark of Urban Attitudes Holdings Ltd.

Distributed by: Urban Attititudes Holdings Ltd.

Great Neck, NY 11023 (516) 206-3672

Made in Peru

PACKAGE LABEL

puresolutions

Hand Sanitizing

ANTISEPTIC WIPES

Benzalkonium Chloride 0.1%

Kills Germs

800 Wet Wipes

8 in. x 6 in. (20.3 cm x 15.2 cm)